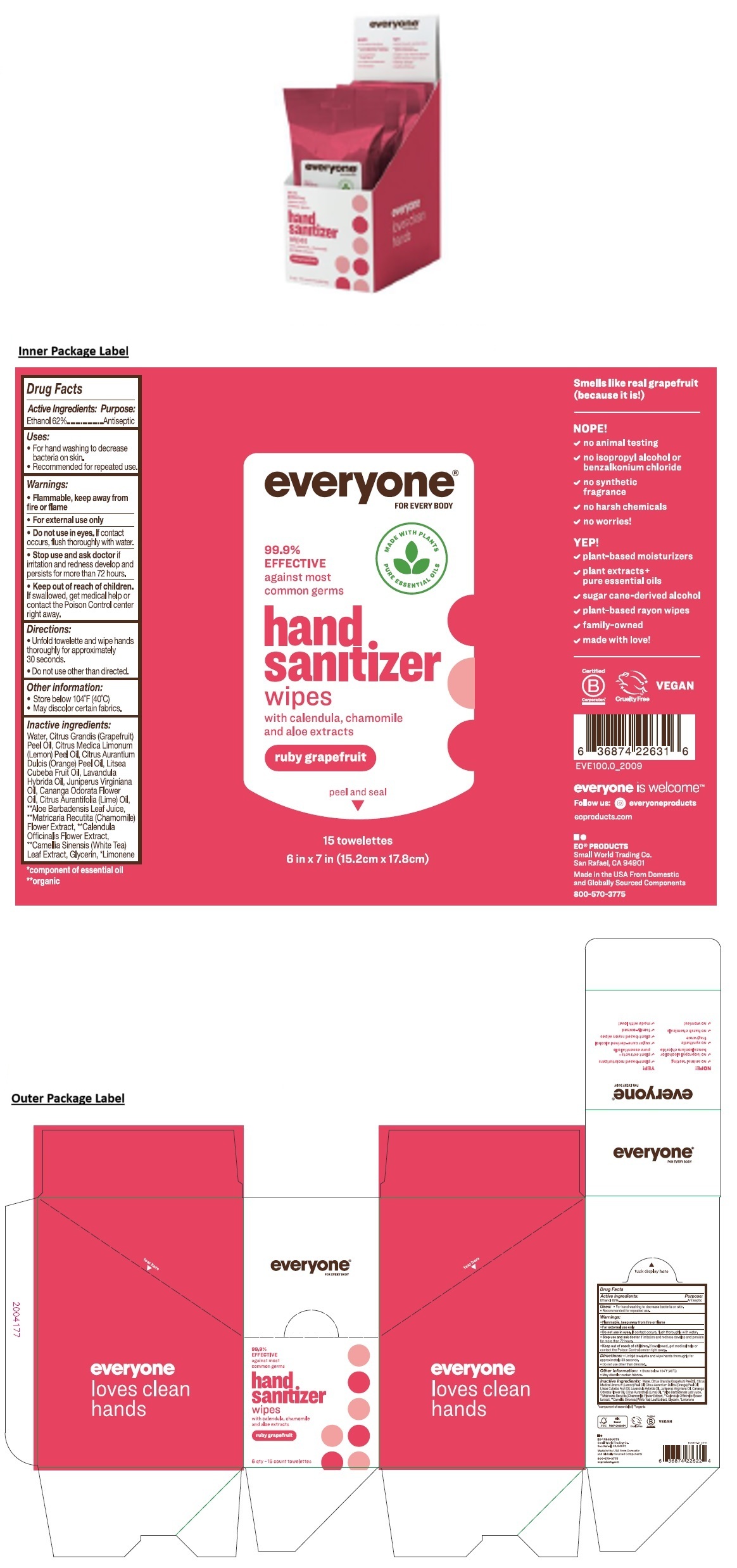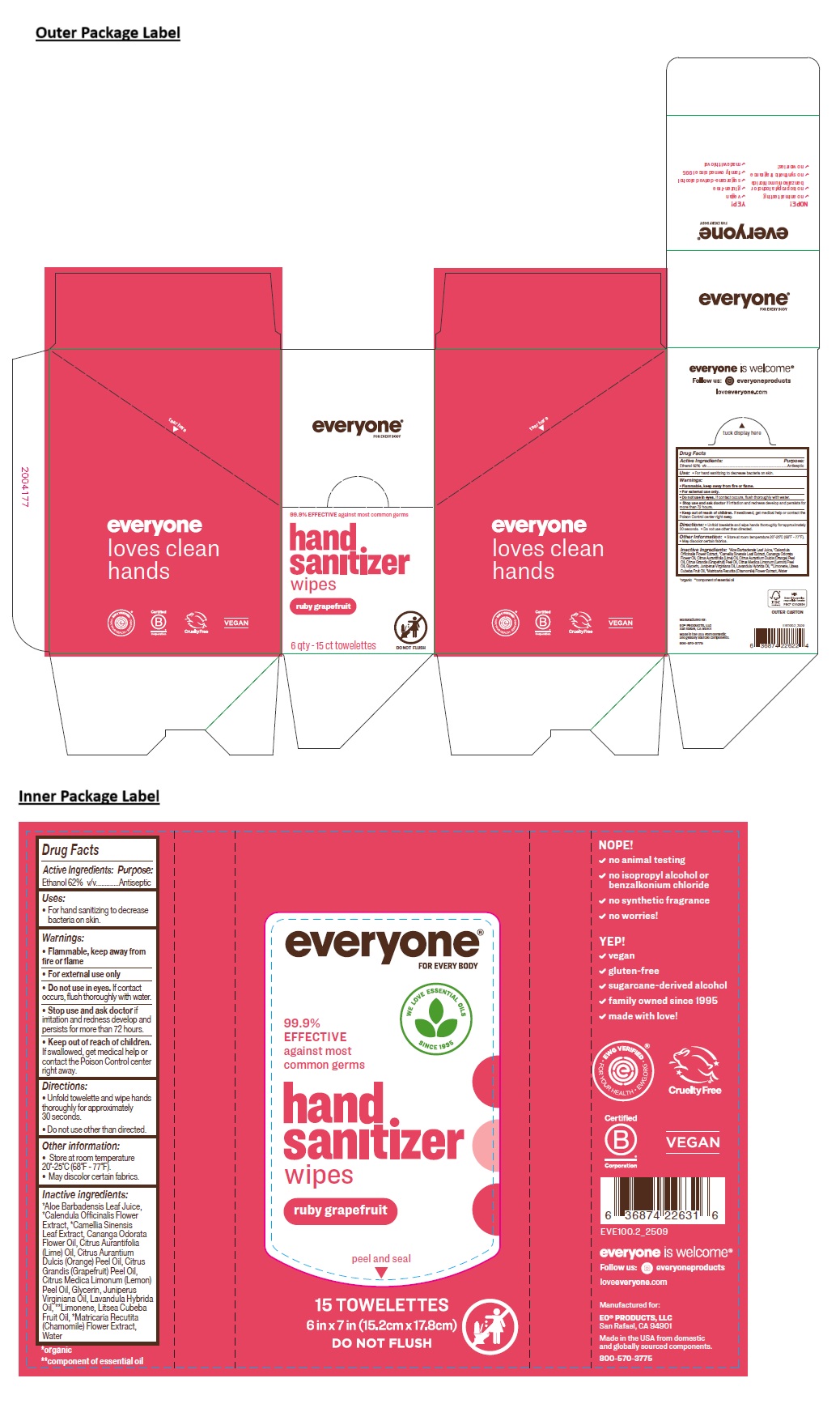 DRUG LABEL: everyone hand sanitizer wipes
NDC: 54748-703 | Form: CLOTH
Manufacturer: EO Products, LLC
Category: otc | Type: HUMAN OTC DRUG LABEL
Date: 20251121

ACTIVE INGREDIENTS: ALCOHOL 62 mL/100 mL
INACTIVE INGREDIENTS: ALOE VERA LEAF JUICE; CALENDULA OFFICINALIS FLOWER; GREEN TEA LEAF; YLANG-YLANG OIL; LIME OIL, COLD PRESSED; ORANGE OIL, COLD PRESSED; CITRUS MAXIMA FRUIT RIND OIL; LEMON OIL, COLD PRESSED; GLYCERIN; JUNIPERUS VIRGINIANA OIL; LAVANDIN OIL; LIMONENE, (+)-; LITSEA OIL; CHAMOMILE; WATER

everyone® FOR EVERY BODY hand sanitizer wipes ruby grapefruit

Active Ingredients:

Ethanol 62% v/v

Purpose:

Antiseptic

Use:

- For hand sanitizing to decrease bacteria on skin.

Warnings:

- Flammable, keep away from fire or flame.
- For external use only.
- Do not use in eyes. If contact occurs, flush thoroughly with water.
- Stop use and ask doctor if irritation and redness develop and persists for more than 72 hours.

- Keep out of reach of children. If swallowed, get medical help or contact the Poison Control center right away.

Directions:

- Unfold towelette and wipe hands thoroughly for approximately 30 seconds. • Do not use other than directed.

Other Information:

- Store at room temperature 20˚-25˚C (68˚F - 77˚F).
- May discolor certain fabrics.

Inactive Ingredients:

*Aloe Barbadensis Leaf Juice, *Calendula Officinalis Flower Extract, *Camellia Sinensis Leaf Extract, Cananga Odorata Flower Oil, Citrus Aurantifolia (Lime) Oil, Citrus Aurantium Dulcis (Orange) Peel Oil, Citrus Grandis (Grapefruit) Peel Oil, Citrus Medica Limonum (Lemon) Peel Oil, Glycerin, Juniperus Virginiana Oil, Lavandula Hybrida Oil, **Limonene, Litsea Cubeba Fruit Oil, *Matricaria Recutita (Chamomile) Flower Extract, Water

*organic **component of essential oil

99.9% EFFECTIVE against most common germs

DO NOT FLUSH

everyone loves clean hands

Cruelty Free

VEGAN

everyone is welcome®

Follow us: everyoneproducts

loveeveryone.com

Manufactured for:

EO® PRODUCTS, LLC
San Rafael, CA 94901
Made in the USA from domestic and globally sourced components.
800-570-3775

WE LOVE ESSENTIAL OILS SINCE 1995

NOPE!

✓ no animal testing

✓ no isopropyl alcohol or benzalkonium chloride

✓ no synthetic fragrance

✓ no harsh chemicals

✓ no worries!

YEP!

✓ gluten-free

✓ sugarcane-derived alcohol

✓ family owned since 1995

✓ made with love!